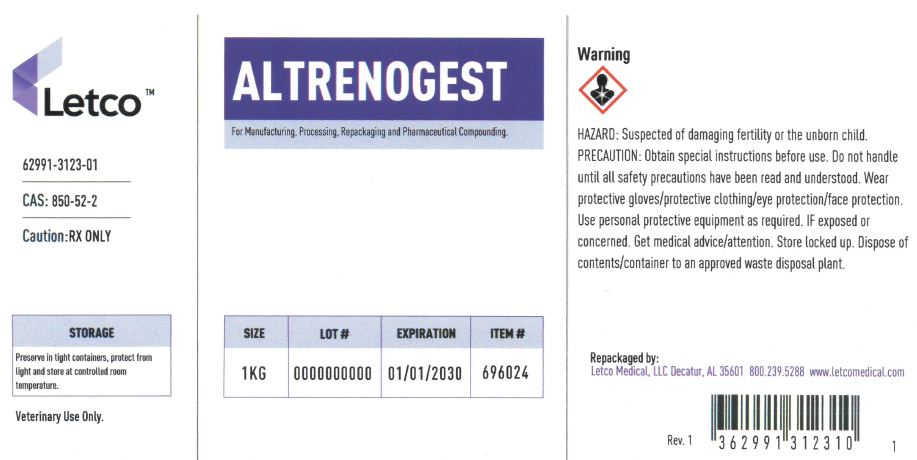 DRUG LABEL: Altrenogest
NDC: 62991-3123 | Form: POWDER
Manufacturer: LETCO MEDICAL, LLC
Category: other | Type: BULK INGREDIENT - ANIMAL DRUG
Date: 20240718

ACTIVE INGREDIENTS: ALTRENOGEST 1 g/1 g

Altrenogest

PACKAGE LABEL

Altrenogest 1kg